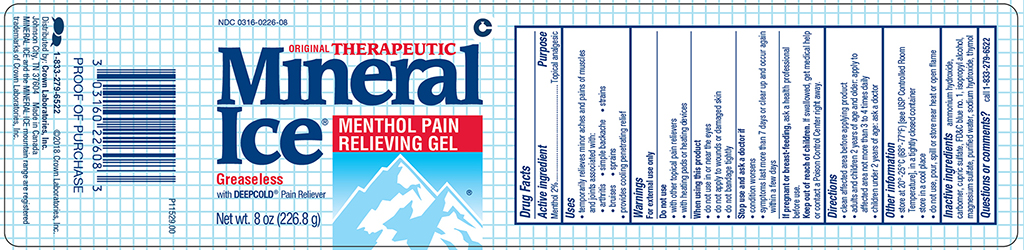 DRUG LABEL: Mineral Ice
NDC: 0316-0226 | Form: GEL
Manufacturer: Crown Laboratories
Category: otc | Type: HUMAN OTC DRUG LABEL
Date: 20260112

ACTIVE INGREDIENTS: MENTHOL 20 mg/1 g
INACTIVE INGREDIENTS: AMMONIA; CARBOMER HOMOPOLYMER TYPE B; CUPRIC SULFATE; FD&C BLUE NO. 1; ISOPROPYL ALCOHOL; MAGNESIUM SULFATE HEPTAHYDRATE; SODIUM HYDROXIDE; THYMOL; WATER

Mineral Ice

Active ingredient

Menthol 2%

Purpose

Topical analgesic

Uses

● temporarily relieves minor aches and pains of muscles and joints associated with:

● arthritis ● simple backache ● strains

- ● bruises ● sprains

● provides cooling penetrating relief

Warnings

For external use only

Do not use

- with other topical pain relievers
- with heating pads or heating devices

When using this product

- do not use in or near the eyes
- do not apply to wounds or damaged skin
- do not bandage tightly

Stop use and ask a doctor if

- condition worsens
- symptoms last more than 7 days or clear up and occur again within a few days

If pregnant or breast-feeding,

ask a health professional before use.

Keep out of reach of children.

If swallowed, get medical help or contact a Poison Control Center right away.

Directions

- clean affected area before applying product
- adults and children 2 years of age and older: apply to affected area not more than 3 to 4 times daily
- children under 2 years of age: ask a doctor

Other information

- store at 20o - 25oC (68o - 77oF) [see USP Controlled Room Temperature], in a tightly closed container
- store in a cool place
- do not use, pour, spill or store near heat or open flame

Inactive ingredients

ammonium hydroxide, carbomer, cupric sulfate, FD&C blue no. 1, isopropyl alcohol, magnesium sulfate, purified water, sodium hydroxide, thymol

Questions or comments?

call 1-833-279-6522

Additional Information Listed on Other Panels

1-833-279-6522 ©Crown Laboratories, Inc.

Distributed by: Crown Laboratories, Inc.

Johnson City, TN 37604 ©2018 Made in Canada.

Mineral Ice and the Mineral Ice mountain range are registered trademarks of Crown Laboratories, Inc.

Principal Display

NDC 0316-0226-08

ORIGINAL THERAPEUTIC

Mineral Ice®

Menthol Pain Relieving Gel

Greaseless with DEEPCOLD® Pain Reliever

Net wt. 8 oz (226.8 g)

P11529.00